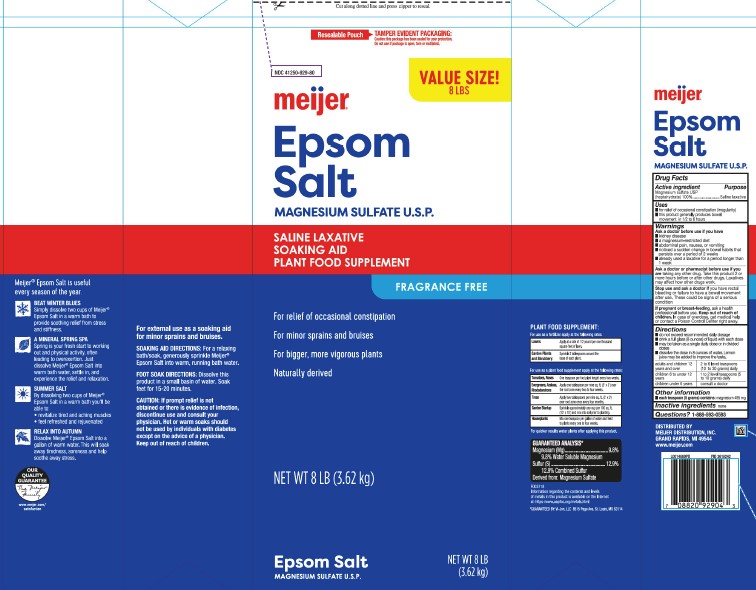 DRUG LABEL: Epsom Salt
NDC: 41250-929 | Form: GRANULE
Manufacturer: Meijer, Inc.
Category: otc | Type: HUMAN OTC DRUG LABEL
Date: 20260219

ACTIVE INGREDIENTS: MAGNESIUM SULFATE HEPTAHYDRATE 1 g/1 g

Meijer 029.003/029AA
Epsom Salt 3 in 1

Claims

meijer

Epsom Salt

MAGNESIUM SULFATE U.S.P.

Active ingredient

Magnesium sulfate USP (heptahydrate) 100%

Purpose

Saline Laxative

Uses

- for relief of occasional constipation (irregularity)
- this product generally produces bowel movement in 1/2 to 6 hours

Warnings

for this product

Ask a doctor before use if you have

- kidney disease
- a magnesium-restricted diet
- abdominal pain, nausea, or vomiting
- noticed a sudden change in bowel habits that persists over a period of 2 weeks
- already used a laxative for a period longer than 1 week

Ask a doctor or pharmacist before use if you are

taking any other drug. Take this product 2 or more hours before or after other drugs. Laxatives may affect how other drugs work.

Stop use and ask a doctor if

you have rectal bleeding or failure to have a bowel movement after use. These could be signs of a serious condition.

If pregnant or breast-feeding,

ask a health professional before use.

Keep out of reach of children.

In case of overdose, get medical help or contact a Poison Control Center right away.

Directions

- do not exceed recommended daily dosage
- drink a full glass (8 ounces) of liquid with each dose
- may be taken as a single daily dose or in divided doses
- dissolve the dose in 8 ounces of water. Lemon juice may be added to improve the taste

adults and children 12 years and over - 2 to 6 level teaspoons (10 to 30 grams) daily

children 6 to under 12 years - 1 to 2 level teaspoons (5 to 10 grams) daily

children under 6 years - consult a doctor

Other information

- each teaspoon (5 grams) contains: magnesium 495 mg

Inactive Ingredient

None

Questions?

1-888-593-0593

Adverse reaction

DISTRIBUTED BY

MEIJER DISTRIBUTION, INC.

GRAND RAPIDS, MI 49544

www.meijer.com

Side Panel

PLANT FOOD SUPPLEMENT:

For use as a fertilizer apply at the following rates:

Lawns- Apply at a rate of 1/2 pound per one thousand square feet of lawn.

Garden Plants and Shrubbery:Sprinkle 2 tablespoons around the base of each plant.

For use as a plant food supplement apply at the following rates:

Tomatoes, Roses- One teaspoon per foot plant height every two weeks.

Evergreens, Azaleas, Rhododendrons- Apply one tablespoon per nine sq. ft. (3' x 3') over the root zone every two to for weeks.

Trees-Apply two tablespoons per nine sq. ft. (3' x3') over root zone once every four months.

Garden Startup- Sprinkle approximately one cup per 100 sq. ft. (10' x 10') and mix into soil prior to planting.

Houseplants-Mix one teaspoon per gallon of water and feed to plants every one to four weeks.

For quicker results water plants after applying this product.

GUARANTEED ANALYSIS*

Magnesium (Mg) 9.8% - 9.8% Soluble Magnesium (Mg)
Sulfur (S) 12.9% - 12.9% Combined Sulfur (S)
Derived from: magnesium sulfate

F003718

Information regarding the contents and levels of metals in this product is available on the Internet at:
http:/www.aapfco.org/metals.html

*GUARANTEED BY: Vi-Jon, Inc 8515 Page Ave. St. Louis, MO 63114

Side panel

For external use as a soaking aid for minor sprains and bruises.

SOAKING AID DIRECTIONS:For a relaxing bath/soak, generously sprinkle Meijer®Epsom Salt into warm, running bath water.

FOOT SOAK DIRECTIONS:Dissolve this product in a small basin of water. Soak feet for 15-20 minutes.

Caution: If prompt relief is not obtained or there is evidence of infection, discontinue use and consult your physician. Hot or warm soaks should not be used by individuals with diabetes except on the advice of a physician. Keep out of reach of children.

Side panel

Meijer®Epsom salt is useful every season of the year.

Beat winter blues

Simply dissolve two cups of Meijer® Epsom Salt in a warm bath to provide soothing relief from stress and stiffness.

A mineral spring spa

Spring is your fresh start to working out and physical activity, often leading to overexertion. Just dissolve Meijer® Epsom Salt into warm bath water, settle in, and experience the relief and relaxation.

Summer Salt

By dissolving two cups of Meijer® Epsom Salt in a warm bath you'll be able to:

- revitalize tired and aching muscles
- feel refreshed and rejuvenated

Relax into autumn

Dissolve Meijer® Epsom Salt into a gallon of warm water. This will soak away tiredness, soreness and help soothe away stress.

OUR QUALITY GUARANTEE

The Meijer Family

www.meijer.com/satisfaction

Principal Panel Display

Cut along dotted line and press zipper to reseal.

Resealable Pouch

Tamper Evident Packaging.

Caution: this package has been sealed for your protection. Do not use if package is open, torn or mutilated.

Value Size! 8 lbs

NDC 41250-929-80

Meijer®

epsom salt

MAGNESIUM SULFATE U.S.P.

saline laxative

soaking aid

plant food supplement

Fragrance Free

For relief of occasional constipation

For minor sprains and bruises

For bigger, more vigorous plants

Naturally derived

NET WT 8 LB (3.62 kg)

Epsom Salt

MAGNESIUM SULFATE U.S.P.

NET WT 8 LB (3.62 kg)